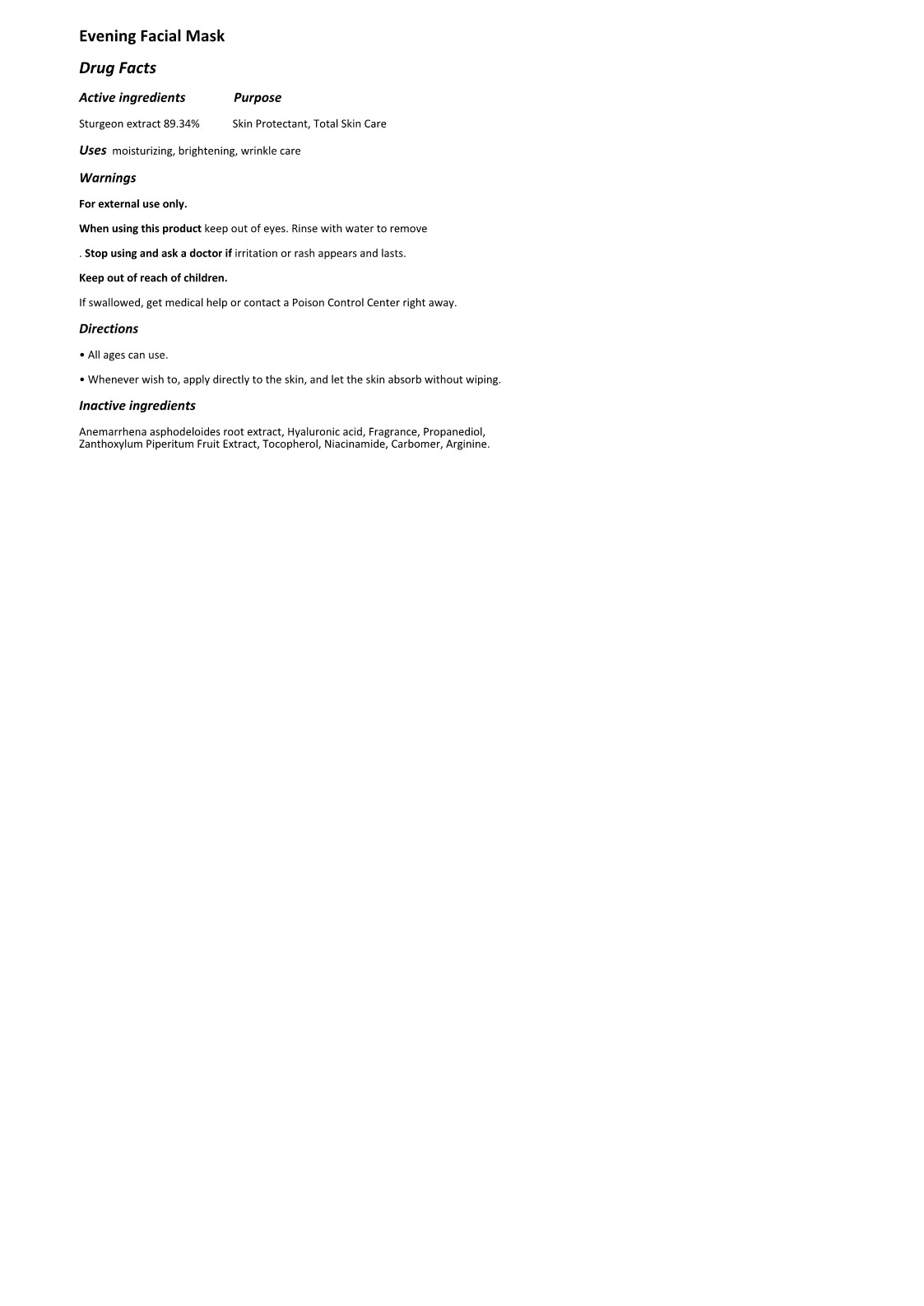 DRUG LABEL: The Zoeun Skin Night Mask
NDC: 83636-604 | Form: LIQUID
Manufacturer: Sturgeonbio Co.,Ltd.
Category: otc | Type: HUMAN OTC DRUG LABEL
Date: 20250120

ACTIVE INGREDIENTS: STURGEON, UNSPECIFIED 89.34 g/100 mL
INACTIVE INGREDIENTS: PROPANEDIOL; ZANTHOXYLUM PIPERITUM FRUIT PULP; ARGININE; FRAGRANCE 13576; NIACINAMIDE; CARBOMER HOMOPOLYMER, UNSPECIFIED TYPE; ANEMARRHENA ASPHODELOIDES ROOT; HYALURONIC ACID; TOCOPHEROL

83636-604 The Zoeun Skin Night Mask

Active Ingredients

Sturgeon extract

Purposes

Skin Protectant, Total Skin Care

Uses

Skin Nourishing, Moisturizing, Brightening, Wrinkle Care

Warnings

For external use only.

Warnings

When using this product keep out of eyes. Rinse with water to remove.

Warnings

Stop using and ask a doctor if irritation or rash appears and lasts.

Warnings

Keep out of reach of children.

If swallowed, get medical help or contact a Poison Control Center right away.

Directions

• All ages can use.

• Whenever wish to, apply directly to the skin, and let the skin absorb without wiping.

Inactive Ingredients

Anemarrhena asphodeloides root extract, Hyaluronic acid, Fragrance, Propanediol, Zanthoxylum Piperitum Fruit Extract, Tocopherol, Niacinamide, Carbomer, Arginine.